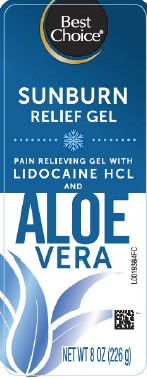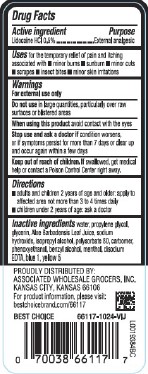 DRUG LABEL: Aloe Vera Gel
NDC: 63941-005 | Form: GEL
Manufacturer: Valu Merchandisers Company
Category: otc | Type: HUMAN OTC DRUG LABEL
Date: 20260216

ACTIVE INGREDIENTS: LIDOCAINE HYDROCHLORIDE 5 mg/1 g
INACTIVE INGREDIENTS: WATER; PROPYLENE GLYCOL; GLYCERIN; ALOE VERA LEAF; SODIUM HYDROXIDE; ISOPROPYL ALCOHOL; POLYSORBATE 80; CARBOMER HOMOPOLYMER, UNSPECIFIED TYPE; PHENOXYETHANOL; BENZYL ALCOHOL; MENTHOL; EDETATE DISODIUM ANHYDROUS; FD&C BLUE NO. 1; FD&C YELLOW NO. 5

Best Choice 005.003/005AE
Sunburn Relief with Aloe

Active ingredient

Lidocaine HCl 0.5%

Purpose

External analgesic

Uses

for the temporary relief of pain and itching associated with

- minor burns
- sunburn
- minor cuts
- scrapes
- insect bites
- minor skin irritations

Warnings

For external use only

Do not use

in large quantities, particularly over raw surfaces or blistered areas

When using this product

avoid contact with the eyes

Stop use and ask a doctor if

condition worsens, or if symptoms persist for more than 7 days or clear up and occur again within a few days

Keep out of reach of children.

If swallowed, get medical help or contact a Poison Control Center right away.

Directions

- adults and children 2 years of age and older: apply to affected area not more than 3 to 4 times daily
- children under 2 years of age: ask a doctor

Inactive ingredients

water, propylene glycol, glycerin, Aloe Barbadensis Leaf Juice, sodium hydroxide, isopropyl alcohol, polysorbate 80, carbomer, phenoxyethanol, benzyl alcohol, menthol, disodium EDTA, blue 1, yellow 5

ADVERSE REACTION

PROUDLY DISTRIBUTED BY:

ASSOCIATED WHOLESALE GROCERS, INC.

KANSAS CITY, KANSAS 66106

For product information, please visit: bestchoicebrand.com/66117

BEST CHOICE 66117-1024-VIJ

principal display panel

Best Choice®

Sunburn

RELIEF GEL

PAIN RELIEVING GEL WITH

LIDOCAINE HCL

AND

ALOE VERA

NET WT 8 OZ (226 g)